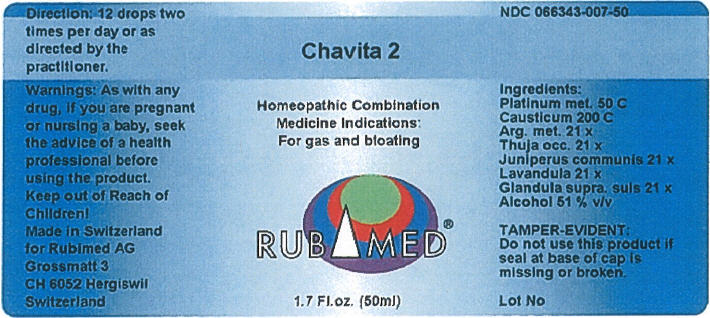 DRUG LABEL: Chavita 2
NDC: 66343-007 | Form: LIQUID
Manufacturer: RUBIMED AG
Category: otc | Type: HUMAN OTC DRUG LABEL
Date: 20150706

ACTIVE INGREDIENTS: PLATINUM 50 [hp_C]/1 mL; CAUSTICUM 200 [hp_C]/1 mL; SILVER CYANIDE 21 [hp_X]/1 mL; THUJA OCCIDENTALIS LEAFY TWIG 21 [hp_X]/1 mL; JUNIPER BERRY 21 [hp_X]/1 mL; LAVANDULA ANGUSTIFOLIA WHOLE 21 [hp_X]/1 mL; SUS SCROFA ADRENAL GLAND 21 [hp_X]/1 mL
INACTIVE INGREDIENTS: Alcohol 0.51 mL/1 mL

Chavita 2

PURPOSE

Homeopathic Combination Medicine Indications: For gas and bloating

Ingredients

INACTIVE INGREDIENT

Platinum met. 50 C
Causticum 200 C
Arg. met. 21 x
Thuja occ. 21 x
Juniperus communis 21 x
Lavandula 21 x
Glandula supra. suis 21 x
Alcohol 51 % v/v

TAMPER-EVIDENT

Do not use this product if seal at base of cap is missing or broken.

Direction

12 drops two times per day or as directed by the practitioner.

Warnings

PREGNANCY OR BREAST FEEDING

As with any drug, if you are pregnant or nursing a baby, seek the advice of a health professional before using the product.

Keep out of Reach of Children!

PRINCIPAL DISPLAY PANEL - 50 mL Bottle Label

Chavita 2

Homeopathic Combination
Medicine Indications:
For gas and bloating

RUBIMED®

1.7 Fl.oz. (50ml)